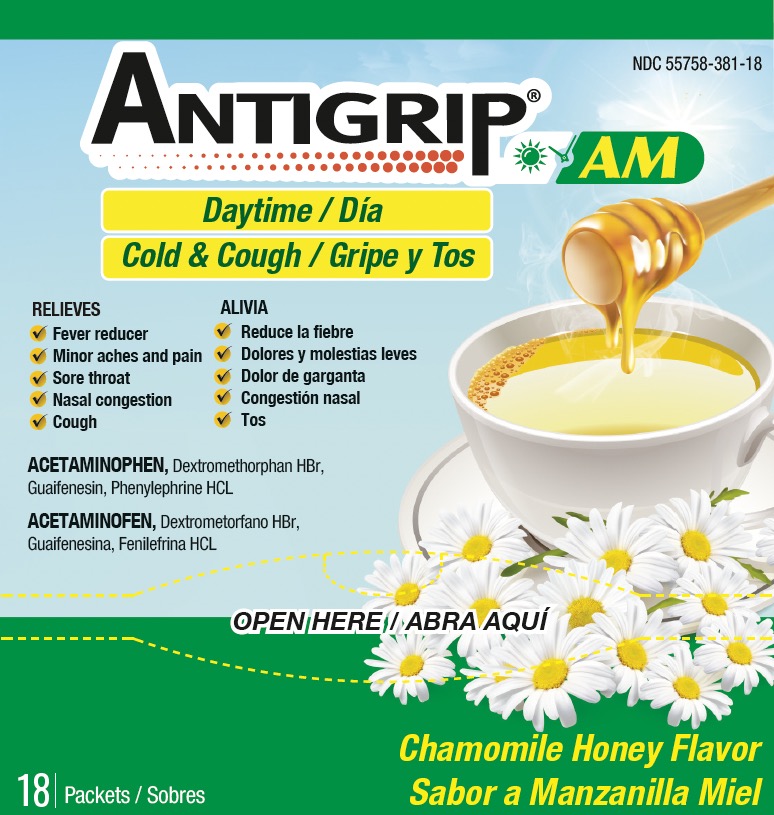 DRUG LABEL: ANTIGRIP
NDC: 55758-381 | Form: POWDER, FOR SOLUTION
Manufacturer: Pharmadel LLC
Category: otc | Type: HUMAN OTC DRUG LABEL
Date: 20240316

ACTIVE INGREDIENTS: GUAIFENESIN 200 mg/1 1; ACETAMINOPHEN 325 mg/1 1; DEXTROMETHORPHAN HYDROBROMIDE 10 mg/1 1; PHENYLEPHRINE HYDROCHLORIDE 5 mg/1 1
INACTIVE INGREDIENTS: ANHYDROUS CITRIC ACID; SILICON DIOXIDE; ISOPROPYL ALCOHOL; MALTODEXTRIN; WATER; ACESULFAME POTASSIUM; ASPARTAME; SODIUM CITRATE; SUCROSE; TRIBASIC CALCIUM PHOSPHATE

Antigrip Daytime Tea C-H (AS)

Active ingredients & Purposes

PURPOSE

Active ingredients (in each packet) | Purposes
Acetaminophen 325 mg………………………………… | Pain reliever/ fever reducer
Dextromethorphan HBr 10 mg…………………………... | Cough suppressant
Guaifenesin 200 mg ..................................... | Expectorant
Phenylephrine HCL 5 mg…….………………………….. | Nasal decongestant

Uses

Temporary relieves common cold/flu symptoms:

- minor aches and pains
- sore throat
- headache
- stuffy nose
- nasal congestion
- cough due to minor throat and bronchial irritation
- and temporarily reduces fever
- helps loosen phlegm (mucus) and thin bronchial secretions to make coughs more productive

Warnings

Liver Warning: This product contains acetaminophen. Severe liver damage may occur if you take

- more than 6 packets in 24 hours, which is the maximum daily amount for this product
- with other drugs containing acetaminophen
- 3 or more alcoholic drinks every day while using this product

Sore throat warning: if sore throat is severe, persists for more than 2 days, is accompanied or followed by fever, headache, rash, nausea, or vomiting, consult a doctor promptly.

Do not use

- with any other drug containing acetaminophen (prescription or nonprescription). If you are not sure whether a drug contains acetaminophen, ask a doctor or pharmacist.
- if you are now taking prescription monoamine oxidase inhibitor (MAOI) (certain drugs for depression, psychiatric, or emotional conditions, or Parkinson's disease), or 2 weeks after stopping the MAOI drug. If you do not know if your prescription drug contains an MAOI, ask a doctor or pharmacist before taking this product

Ask a doctor before use if you have

- liver disease
- heart disease
- high blood pressure
- thyroid disease
- diabetes
- glaucoma
- a cough that is accompanied by excessive phlegm (mucus)
- a persistent or chronic cough such as occurs with smoking, asthma, chronic bronchitis, or emphysema
- difficulty urinating due to an enlarged prostate gland

Ask a doctor or pharmacist before use if you are

- taking the blood thinning drug warfarin

When using this product

- do not exceed recommended dosage

Stop use and ask doctor if

- nervousness, dizziness, or sleeplessness occurs
- redness or swelling is present
- pain or nasal congestion gets worse or lasts more than 7 days
- fever gets worse or lasts more than 3 days
- any new symptoms occur
- a persistent cough or symptoms do not improve within 7 days, tends to recur, or is accompanied by fever, rash, or persistent headache. These could be signs of a serious condition.

If pregnant or breast-feeding,

ask a health professional before use.

KEEP OUT OF REACH OF CHILDREN.

In case of an accidental overdose, get medical help or contact a Poison Control Center right away. Prompt medical attention is critical for adults as well as for children even if you do not notice any signs or symptoms.

Directions

- dissolve one packet in an 8oz. glass of hot water. If using a microwave; add content into a glass of cool water and stir briskly before and after heating. Do not overheat.
- sip while hot and consume the entire drink within 10-15 minutes

Age | Dose
adults and children 12 years of age and over | one (1) packet every 4 hours,; take every 4 hours; do not exceed 6 packets in a 24 hours
children under 12 years of age | do not use

Other information

- each packet contains: potassium 10 mg, sodium 27 mg
- phenylketonurics: contains phenylalanine 13 mg per packet
- store at room temperature 68-77°F (20-25°C)
- do not use if packet is punctured or torn

Inactive ingredients

acesulfame potassium, anhydrous citric acid, aspartame, chamomile honey flavors, isopropyl alcohol, maltodextrin, silicon dioxide, sodium citrate, sucrose, tribasic calcium phosphate, water

Questions & comments?

1-866-359-3478 (M-F) 9 AM to 5 PM EST or www.pharmadel.com

Dist. by:

PHARMADEL LLC

New Castle, DE, 19720